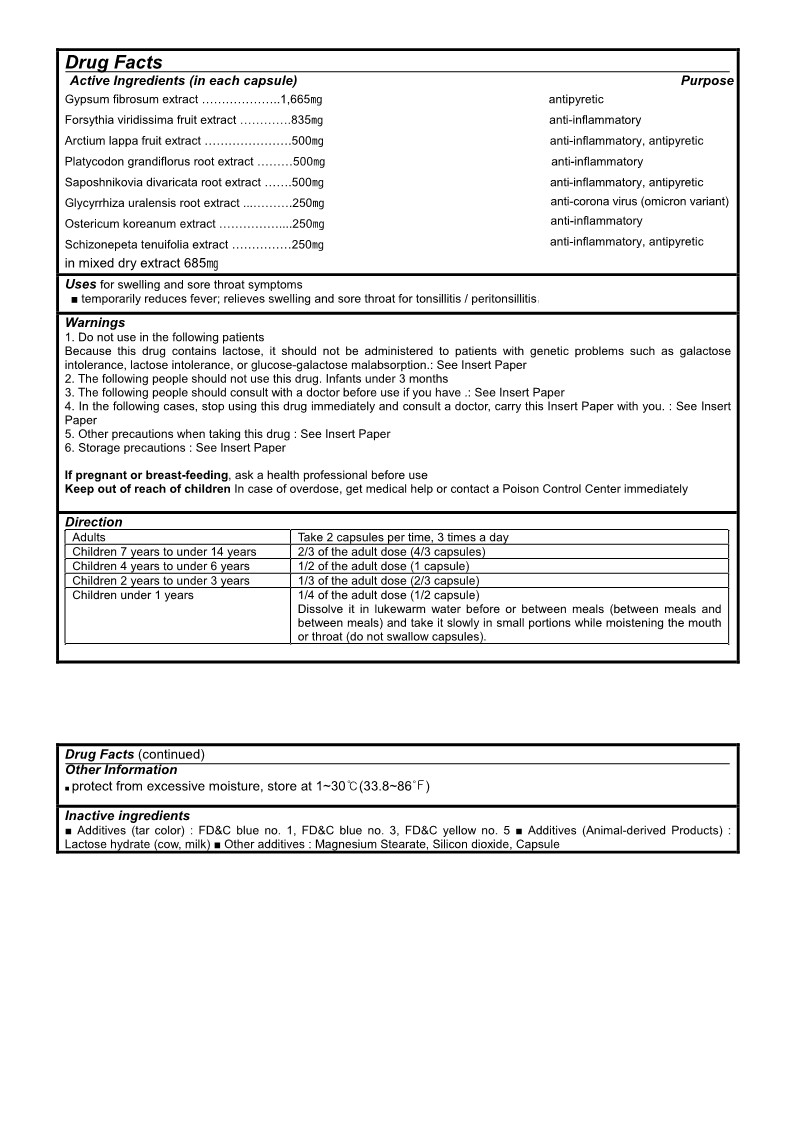 DRUG LABEL: Stomasin
NDC: 82871-301 | Form: CAPSULE, COATED
Manufacturer: MedicareBio.Co.Ltd
Category: homeopathic | Type: HUMAN OTC DRUG LABEL
Date: 20231228

ACTIVE INGREDIENTS: OSTERICUM GROSSESERRATUM ROOT 250 mg/1 1; CALCIUM SULFATE, UNSPECIFIED FORM 1665 mg/1 1; FORSYTHIA VIRIDISSIMA FRUIT 835 mg/1 1; ARCTIUM LAPPA FRUIT 500 mg/1 1; PLATYCODON GRANDIFLORUM ROOT 500 mg/1 1; SAPOSHNIKOVIA DIVARICATA ROOT 500 mg/1 1; NEPETA TENUIFOLIA FLOWERING TOP 250 mg/1 1; GLYCYRRHIZA URALENSIS ROOT 250 mg/1 1
INACTIVE INGREDIENTS: FD&C YELLOW NO. 5; MAGNESIUM STEARATE; FD&C BLUE NO. 1; LACTOSE MONOHYDRATE; SILICON DIOXIDE; GELATIN, UNSPECIFIED

82871-301-01 Stomasin

Active Ingredients

Gypsum fibrosum extract, Forsythia viridissima fruit extract, Arctium lappa fruit extract, Platycodon grandiflorus root extract, Saposhnikovia divaricata root extract, Glycyrrhiza uralensis root extract, Ostericum koreanum extract, Schizonepeta tenuifolia extract

Purpose

antipyretic, anti-inflammatory, anti-corona virus (omicron variant)

Uses

for swelling and sore throat symptoms

temporarily reduces fever; relieves swelling and sore throat for tonsillitis / peritonsillitis

Warnings

Do not use in the following patients
Because this drug contains lactose, it should not be administered to patients with genetic problems such as galactose intolerance, lactose intolerance, or glucose-galactose malabsorption.: See Insert Paper

Warnings

Keep out of reach of children

Warnings

In the following cases, stop using this drug immediately and consult a doctor, carry this Insert Paper with you. : See Insert Paper

Warnings

The following people should not use this drug. Infants under 3 months

The following people should consult with a doctor before use if you have .: See Insert Paper

Warnings

Storage precautions : See Insert Paper

If pregnant or breast-feeding, ask a health professional before use

In case of overdose, get medical help or contact a Poison Control Center immediately

Directions

Adults Take 2 capsules per time, 3 times a day
Children 7 years to under 14 years 2/3 of the adult dose (4/3 capsules)
Children 4 years to under 6 years 1/2 of the adult dose (1 capsule)
Children 2 years to under 3 years 1/3 of the adult dose (2/3 capsule)
Children under 1 years 1/4 of the adult dose (1/2 capsule)
Dissolve it in lukewarm water before or between meals (between meals and between meals) and take it slowly in small portions while moistening the mouth or throat (do not swallow capsules).

Other Information

protect from excessive moisture, store at 1~30℃(33.8~86℉)

Inactive Ingredients

FD&C blue no.1, FD&C blue no.3, FD&C yellow no.5, lactose hydrate (cow, milk), magnesium stearate, silicon dioxide, gelatin